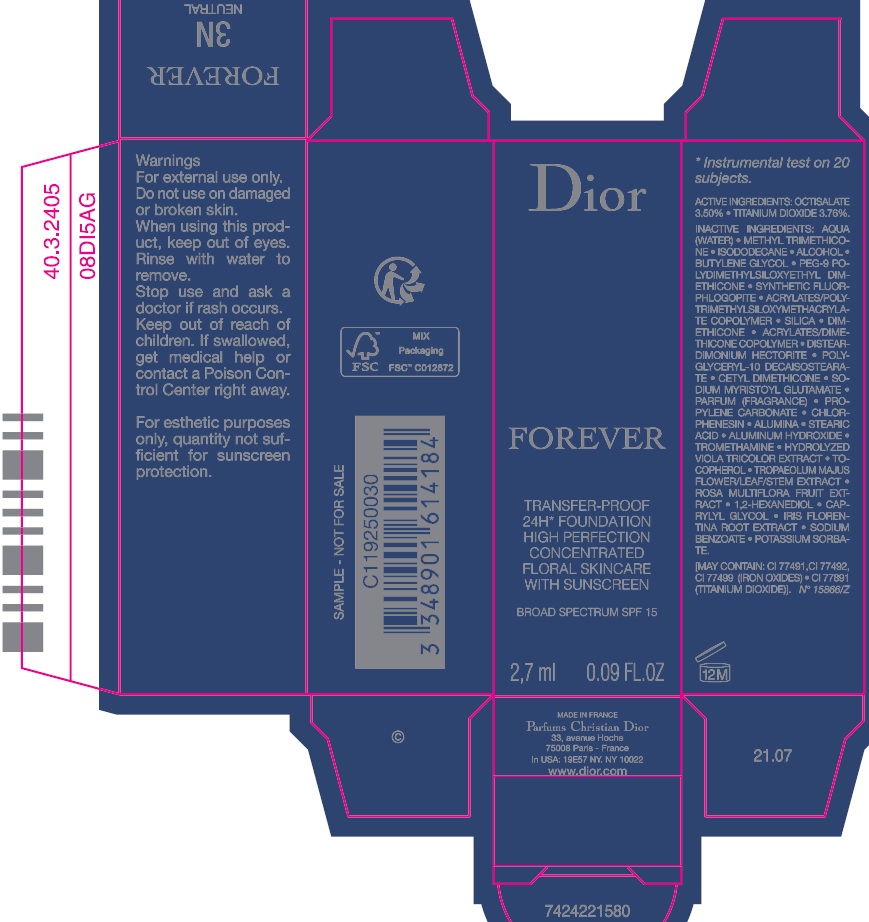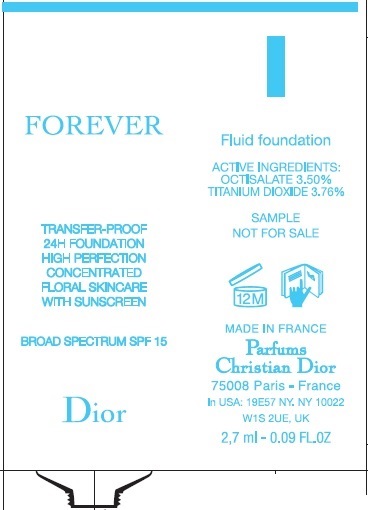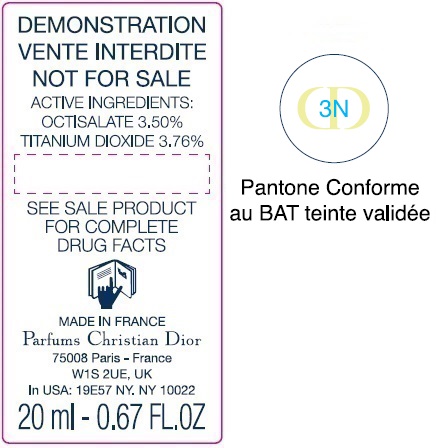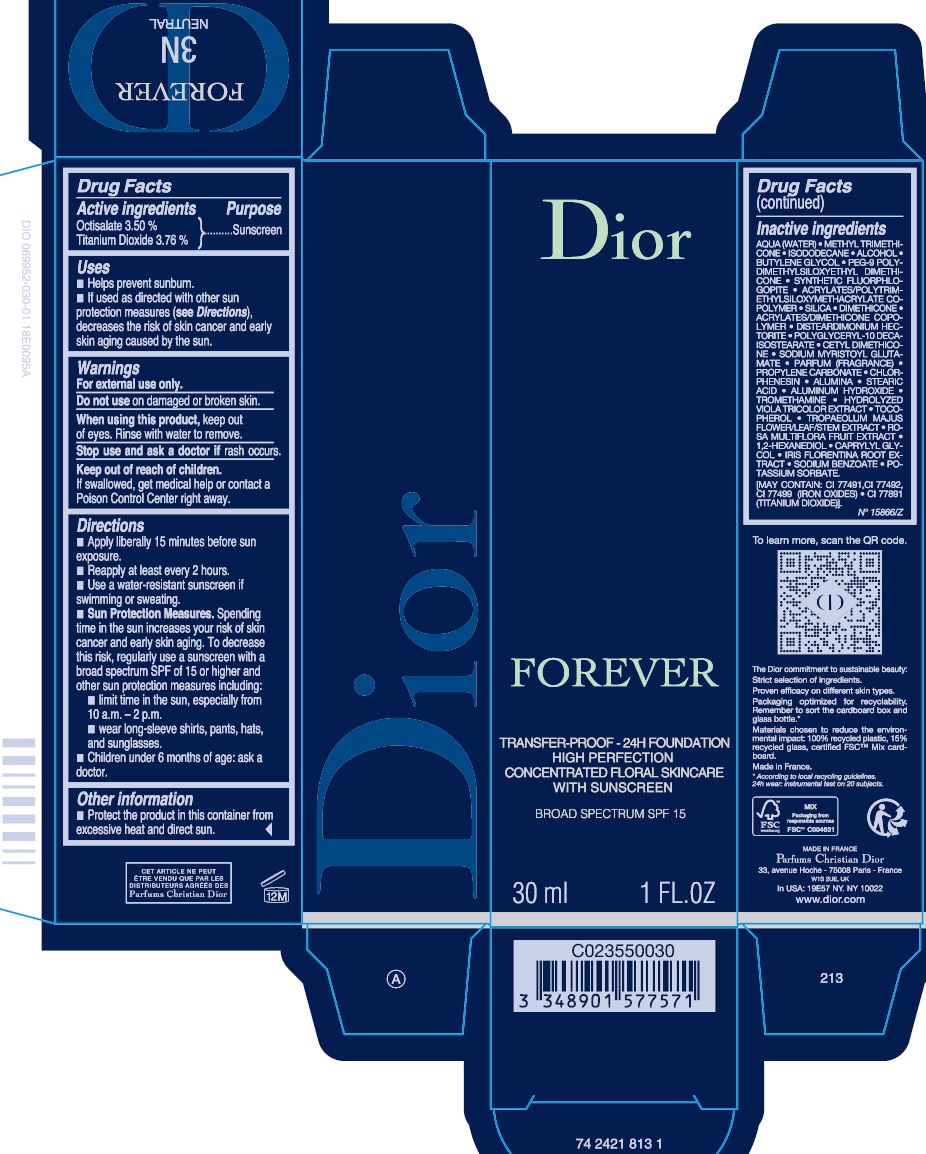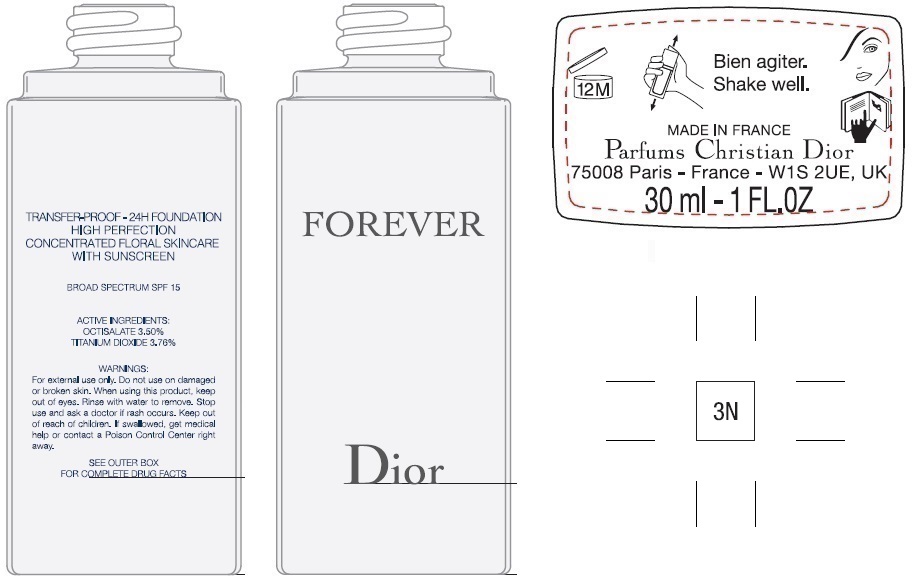 DRUG LABEL: FOREVER Transfer-proof 24h foundation High perfection Concentrated floral skincare with sunscreen Broad spectrum SPF 15 3N
NDC: 61957-3022 | Form: EMULSION
Manufacturer: Parfums Christian Dior
Category: otc | Type: HUMAN OTC DRUG LABEL
Date: 20251219

ACTIVE INGREDIENTS: OCTISALATE 35 mg/1 mL; TITANIUM DIOXIDE 37.6 mg/1 mL
INACTIVE INGREDIENTS: WATER; METHYL TRIMETHICONE; ISODODECANE; ALCOHOL; BUTYLENE GLYCOL; PEG-9 POLYDIMETHYLSILOXYETHYL DIMETHICONE; SILICON DIOXIDE; DIMETHICONE; 2-ETHYLHEXYL ACRYLATE, METHACRYLATE, METHYL METHACRYLATE, OR BUTYL METHACRYLATE/HYDROXYPROPYL DIMETHICONE COPOLYMER (30000-300000 MW); DISTEARDIMONIUM HECTORITE; SODIUM MYRISTOYL GLUTAMATE; PROPYLENE CARBONATE; CHLORPHENESIN; ALUMINUM OXIDE; STEARIC ACID; ALUMINUM HYDROXIDE; TROMETHAMINE; TOCOPHEROL; TROPAEOLUM MAJUS FLOWERING TOP; ROSA MULTIFLORA FRUIT; 1,2-HEXANEDIOL; CAPRYLYL GLYCOL; IRIS X GERMANICA NOTHOVAR. FLORENTINA ROOT; SODIUM BENZOATE; POTASSIUM SORBATE

FOREVER Transfer-proof - 24h foundation High perfection Concentrated floral skincare with sunscreen Broad spectrum SPF 15 3N

Active ingredients

Octinoxate 3.50 %

Titanium Dioxide 3.76 %

Purpose

Sunscreen

Uses

- Helps prevent sunburn.
- If used as directed with other sun protection measures (), decreases the risk of skin cancer and early skin aging caused by the sun. see Directions

Warnings

For external use only.

Do not use

on damaged or broken skin.

When using this product,

keep out of eyes. Rinse with water to remove.

Stop use and ask a doctor if

rash occurs.

Keep out of reach of children.

If swallowed, get medical help or contact a Poison Control Center right away.

Directions

- Apply liberally 15 minutes before sun exposure.
- Reapply at least every 2 hours.
- Use a water-resistant sunscreen if swimming or sweating.
- Spending time in the sun increases your risk of skin cancer and early skin aging. To decrease this risk, regularly use a sunscreen with a broad spectrum SPF of 15 or higher and other sun protection measures including: Sun Protection Measures.
- limit time in the sun, especially from 10 a.m. - 2 p.m.
- wear long-sleeve shirts, pants, hats, and sunglasses.
- Children under 6 months of age: ask a doctor.

Other information

- Protect the product in this container from excessive heat and direct sun.

Inactive ingredients

AQUA (WATER) • METHYL TRIMETHICONE • ISODODECANE • ALCOHOL • BUTYLENE GLYCOL • PEG-9 POLYDIMETHYLSILOXYETHYL DIMETHICONE • SYNTHETIC FLUORPHLOGOPITE • ACRYLATES/POLYTRIMETHYLSILOXYMETHACRYLATE COPOLYMER • SILICA • DIMETHICONE • ACRYLATES/DIMETHICONE COPOLYMER • DISTEARDIMONIUM HECTORITE • POLYGLYCERYL-10 DECAISOSTEARATE • CETYL DIMETHICONE • SODIUM MYRISTOYL GLUTAMATE • PARFUM (FRAGRANCE) • PROPYLENE CARBONATE • CHLORPHENESIN • ALUMINA • STEARIC ACID • ALUMINUM HYDROXIDE • TROMETHAMINE • HYDROLYZED VIOLA TRICOLOR EXTRACT • TOCOPHEROL • TROPAEOLUM MAJUS FLOWER/LEAF/STEM EXTRACT • ROSA MULTIFLORA FRUIT EXTRACT • 1,2-HEXANEDIOL • CAPRYLYL GLYCOL • IRIS FLORENTINA ROOT EXTRACT • SODIUM BENZOATE • POTASSIUM SORBATE. [MAY CONTAIN : CI 77491, CI 77492, CI 77499 (IRON OXIDES), CI 77891 (TITANIUM DIOXIDE)].

N° 15866/Z